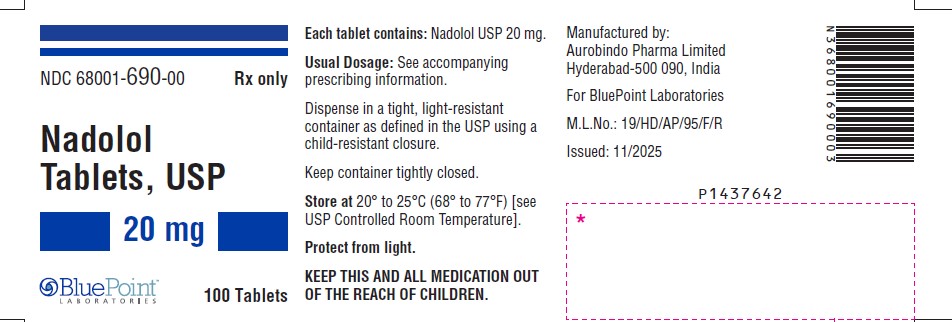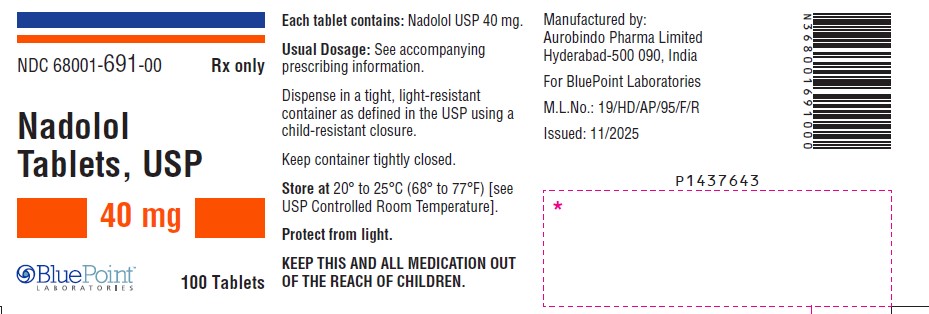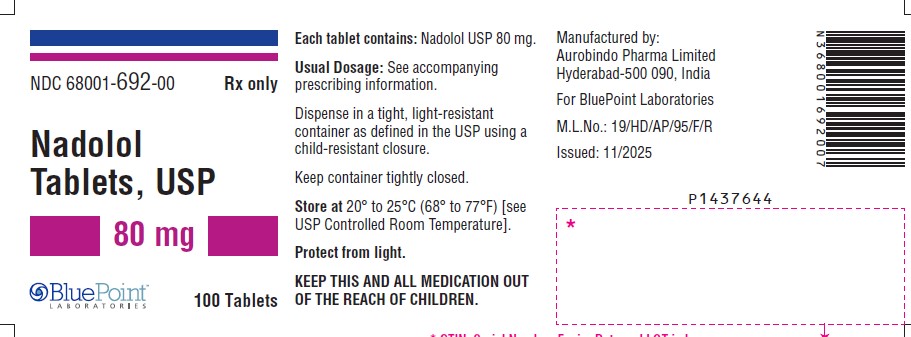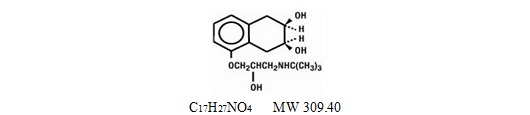 DRUG LABEL: Nadolol
NDC: 68001-690 | Form: TABLET
Manufacturer: BluePoint Laboratories
Category: prescription | Type: HUMAN PRESCRIPTION DRUG LABEL
Date: 20260225

ACTIVE INGREDIENTS: NADOLOL 20 mg/1 1
INACTIVE INGREDIENTS: ANHYDROUS CITRIC ACID; STARCH, CORN; FD&C BLUE NO. 2; MAGNESIUM STEARATE; MICROCRYSTALLINE CELLULOSE 101; MICROCRYSTALLINE CELLULOSE 112; POVIDONE K90

Nadolol Tablets, USP
Rx only

DESCRIPTION

Nadolol tablets USP are a synthetic nonselective beta-adrenergic receptor blocking agent designated chemically as 1-(tert-butylamino)-3-[(5,6,7,8-tetrahydro- cis-6,7-dihydroxy-1-naphthyl)oxy]-2-propanol. Structural formula:

Nadolol is a white to off-white powder. It is soluble in methanol, sparingly soluble in ethanol, slightly soluble in acetone and isopropyl alcohol, very slightly soluble in water pH 2, pH 7 and pH 10.

Nadolol tablets USP are available for oral administration as 20 mg, 40 mg, and 80 mg tablets. Inactive ingredients: citric acid anhydrous, corn starch, FD&C Blue No. 2, magnesium stearate, microcrystalline cellulose and povidone.

CLINICAL PHARMACOLOGY

Nadolol is a nonselective beta-adrenergic receptor blocking agent. Clinical pharmacology studies have demonstrated beta-blocking activity by showing (1) reduction in heart rate and cardiac output at rest and on exercise, (2) reduction of systolic and diastolic blood pressure at rest and on exercise, (3) inhibition of isoproterenol-induced tachycardia, and (4) reduction of reflex orthostatic tachycardia.

Nadolol specifically competes with beta-adrenergic receptor agonists for available beta receptor sites; it inhibits both the beta1receptors located chiefly in cardiac muscle and the beta2receptors located chiefly in the bronchial and vascular musculature, inhibiting the chronotropic, inotropic, and vasodilator responses to beta-adrenergic stimulation proportionately. Nadolol has no intrinsic sympathomimetic activity and, unlike some other beta-adrenergic blocking agents, nadolol has little direct myocardial depressant activity and does not have an anesthetic-like membrane-stabilizing action. Animal and human studies show that nadolol slows the sinus rate and depresses AV conduction. In dogs, only minimal amounts of nadolol were detected in the brain relative to amounts in blood and other organs and tissues. Nadolol has low lipophilicity as determined by octanol/water partition coefficient, a characteristic of certain beta-blocking agents that has been correlated with the limited extent to which these agents cross the blood-brain barrier, their low concentration in the brain, and low incidence of CNS-related side effects.

In controlled clinical studies, nadolol at doses of 40 to 320 mg/day has been shown to decrease both standing and supine blood pressure, the effect persisting for approximately 24 hours after dosing.

The mechanism of the antihypertensive effects of beta-adrenergic receptor blocking agents has not been established; however, factors that may be involved include (1) competitive antagonism of catecholamines at peripheral (non-CNS) adrenergic neuron sites (especially cardiac) leading to decreased cardiac output, (2) a central effect leading to reduced tonic-sympathetic nerve outflow to the periphery, and (3) suppression of renin secretion by blockade of the beta-adrenergic receptors responsible for renin release from the kidneys.

While cardiac output and arterial pressure are reduced by nadolol therapy, renal hemodynamics are stable, with preservation of renal blood flow and glomerular filtration rate.

By blocking catecholamine-induced increases in heart rate, velocity and extent of myocardial contraction, and blood pressure, nadolol generally reduces the oxygen requirements of the heart at any given level of effort, making it useful for many patients in the long-term management of angina pectoris. On the other hand, nadolol can increase oxygen requirements by increasing left ventricular fiber length and end diastolic pressure, particularly in patients with heart failure.

Although beta-adrenergic receptor blockade is useful in treatment of angina and hypertension, there are also situations in which sympathetic stimulation is vital. For example, in patients with severely damaged hearts, adequate ventricular function may depend on sympathetic drive. Beta-adrenergic blockade may worsen AV block by preventing the necessary facilitating effects of sympathetic activity on conduction. Beta2-adrenergic blockade results in passive bronchial constriction by interfering with endogenous adrenergic bronchodilator activity in patients subject to bronchospasm and may also interfere with exogenous bronchodilators in such patients.

Absorption of nadolol after oral dosing is variable, averaging about 30 percent. Peak serum concentrations of nadolol usually occur in three to four hours after oral administration and the presence of food in the gastrointestinal tract does not affect the rate or extent of nadolol absorption. Approximately 30 percent of the nadolol present in serum is reversibly bound to plasma protein.

Unlike many other beta-adrenergic blocking agents, nadolol is not metabolized by the liver and is excreted unchanged, principally by the kidneys.

The half-life of therapeutic doses of nadolol is about 20 to 24 hours, permitting once-daily dosage. Because nadolol is excreted predominantly in the urine, its half-life increases in renal failure (see PRECAUTIONS and DOSAGE AND ADMINISTRATION). Steady-state serum concentrations of nadolol are attained in six to nine days with once-daily dosage in persons with normal renal function. Because of variable absorption and different individual responsiveness, the proper dosage must be determined by titration.

Exacerbation of angina and, in some cases, myocardial infarction and ventricular dysrhythmias have been reported after abrupt discontinuation of therapy with beta-adrenergic blocking agents in patients with coronary artery disease. Abrupt withdrawal of these agents in patients without coronary artery disease has resulted in transient symptoms, including tremulousness, sweating, palpitation, headache, and malaise. Several mechanisms have been proposed to explain these phenomena, among them increased sensitivity to catecholamines because of increased numbers of beta receptors.

INDICATIONS AND USAGE

Angina Pectoris

Nadolol tablets are indicated for the long-term management of patients with angina pectoris.

Hypertension

Nadolol tablets are indicated for the treatment of hypertension, to lower blood pressure. Lowering blood pressure reduces the risk of fatal and nonfatal cardiovascular events, primarily strokes and myocardial infarctions. These benefits have been seen in controlled trials of antihypertensive drugs from a wide variety of pharmacologic classes including the class to which this drug principally belongs. There are no controlled trials demonstrating risk reduction with nadolol tablets.

Control of high blood pressure should be part of comprehensive cardiovascular risk management, including, as appropriate, lipid control, diabetes management, antithrombotic therapy, smoking cessation, exercise, and limited sodium intake. Many patients will require more than one drug to achieve blood pressure goals. For specific advice on goals and management, see published guidelines, such as those of the National High Blood Pressure Education Program’s Joint National Committee on Prevention, Detection, Evaluation, and Treatment of High Blood Pressure (JNC).

Numerous antihypertensive drugs, from a variety of pharmacologic classes and with different mechanisms of action, have been shown in randomized controlled trials to reduce cardiovascular morbidity and mortality, and it can be concluded that it is blood pressure reduction, and not some other pharmacologic property of the drugs, that is largely responsible for those benefits. The largest and most consistent cardiovascular outcome benefit has been a reduction in the risk of stroke, but reductions in myocardial infarction and cardiovascular mortality also have been seen regularly.

Elevated systolic or diastolic pressure causes increased cardiovascular risk, and the absolute risk increase per mmHg is greater at higher blood pressures, so that even modest reductions of severe hypertension can provide substantial benefit. Relative risk reduction from blood pressure reduction is similar across populations with varying absolute risk, so the absolute benefit is greater in patients who are at higher risk independent of their hypertension (for example, patients with diabetes or hyperlipidemia), and such patients would be expected to benefit from more aggressive treatment to a lower blood pressure goal.

Some antihypertensive drugs have smaller blood pressure effects (as monotherapy) in black patients, and many antihypertensive drugs have additional approved indications and effects (e.g., on angina, heart failure, or diabetic kidney disease). These considerations may guide selection of therapy.

Nadolol tablets may be used alone or in combination with other antihypertensive agents, especially thiazide-type diuretics.

CONTRAINDICATIONS

Nadolol is contraindicated in bronchial asthma, sinus bradycardia and greater than first degree conduction block, cardiogenic shock, and overt cardiac failure (see WARNINGS).

WARNINGS

Cardiac Failure

Sympathetic stimulation may be a vital component supporting circulatory function in patients with congestive heart failure, and its inhibition by beta-blockade may precipitate more severe failure. Although beta-blockers should be avoided in overt congestive heart failure, if necessary, they can be used with caution in patients with a history of failure who are well-compensated, usually with digitalis and diuretics. Beta-adrenergic blocking agents do not abolish the inotropic action of digitalis on heart muscle.

IN PATIENTS WITHOUT A HISTORY OF HEART FAILURE, continued use of beta-blockers can, in some cases, lead to cardiac failure. Therefore, at the first sign or symptom of heart failure, the patient should be digitalized and/or treated with diuretics, and the response observed closely, or nadolol should be discontinued (gradually, if possible).

Exacerbation of Ischemic Heart Disease Following Abrupt Withdrawal –Hypersensitivity to catecholamines has been observed in patients withdrawn from beta-blocker therapy; exacerbation of angina and, in some cases, myocardial infarction have occurred after abruptdiscontinuation of such therapy. When discontinuing chronically administered nadolol, particularly in patients with ischemic heart disease, the dosage should be gradually reduced over a period of one to two weeks and the patient should be carefully monitored. If angina markedly worsens or acute coronary insufficiency develops, nadolol administration should be reinstituted promptly, at least temporarily, and other measures appropriate for the management of unstable angina should be taken. Patients should be warned against interruption or discontinuation of therapy without the physician's advice. Because coronary artery disease is common and may be unrecognized, it may be prudent not to discontinue nadolol therapy abruptly even in patients treated only for hypertension.

Nonallergic Bronchospasm (e.g., chronic bronchitis, emphysema)

PATIENTS WITH BRONCHOSPASTIC DISEASES SHOULD IN GENERAL NOT RECEIVE BETA-BLOCKERS. Nadolol should be administered with caution since it may block bronchodilation produced by endogenous or exogenous catecholamine stimulation of beta2receptors.

Major Surgery

Chronically administered beta-blocking therapy should not be routinely withdrawn prior to major surgery; however, the impaired ability of the heart to respond to reflex adrenergic stimuli may augment the risks of general anesthesia and surgical procedures.

Diabetes and Hypoglycemia

Beta blockers may prevent early warning signs of hypoglycemia, such as tachycardia, and increase the risk for severe or prolonged hypoglycemia at any time during treatment, especially in patients with diabetes mellitus or children and patients who are fasting (i.e., surgery, not eating regularly, or are vomiting). If severe hypoglycemia occurs, patients should be instructed to seek emergency treatment.

Beta-blockade also reduces the release of insulin in response to hyperglycemia; therefore, it may be necessary to adjust the dose of antidiabetic drugs.

Thyrotoxicosis

Beta-adrenergic blockade may mask certain clinical signs (e.g., tachycardia) of hyperthyroidism. Patients suspected of developing thyrotoxicosis should be managed carefully to avoid abrupt withdrawal of beta-adrenergic blockade which might precipitate a thyroid storm.

PRECAUTIONS

Impaired Renal Function

Nadolol should be used with caution in patients with impaired renal function (see DOSAGE AND ADMINISTRATION).

INFORMATION FOR PATIENTS

Interruption or Discontinuation of Therapy

Patients, especially those with evidence of coronary artery insufficiency, should be warned against interruption or discontinuation of nadolol therapy without the physician's advice. Although cardiac failure rarely occurs in properly selected patients, patients being treated with beta-adrenergic blocking agents should be advised to consult the physician at the first sign or symptom of impending failure. The patient should also be advised of a proper course in the event of an inadvertently missed dose.

Hypoglycemia
Inform patients or caregivers that there is a risk of hypoglycemia when nadolol is given to patients who are fasting or who are vomiting. Monitor for symptoms of hypoglycemia.

DRUG INTERACTIONS

When administered concurrently, the following drugs may interact with beta-adrenergic receptor blocking agents:

Anesthetics, general -exaggeration of the hypotension induced by general anesthetics (see WARNINGS, Major Surgery).

Antidiabetic drugs (oral agents and insulin) -hypoglycemia or hyperglycemia; adjust dosage of antidiabetic drug accordingly (see WARNINGS, Diabetes and Hypoglycemia).

Catecholamine-depleting drugs (e.g., reserpine) -additive effect; monitor closely for evidence of hypotension and/or excessive bradycardia (e.g., vertigo, syncope, postural hypotension).

Digitalis glycosides-Both digitalis glycosides and beta-blockers slow atrioventricular conduction and decrease heart rate. Concomitant use can increase the risk of bradycardia.

Response to Treatment for Anaphylactic Reaction -While taking beta-blockers, patients with a history of severe anaphylactic reaction to a variety of allergens may be more reactive to repeated challenge, either accidental, diagnostic, or therapeutic. Such patients may be unresponsive to the usual doses of epinephrine used to treat allergic reaction.

CARCINOGENESIS, MUTAGENESIS, IMPAIRMENT OF FERTILITY

In chronic oral toxicologic studies (one to two years) in mice, rats, and dogs, nadolol did not produce any significant toxic effects. In two-year oral carcinogenic studies in rats and mice, nadolol did not produce any neoplastic, preneoplastic, or non-neoplastic pathologic lesions. In fertility and general reproductive performance studies in rats, nadolol caused no adverse effects.

PREGNANCY

In animal reproduction studies with nadolol, evidence of embryo- and fetotoxicity was found in rabbits, but not in rats or hamsters, at doses 5 to 10 times greater (on a mg/kg basis) than the maximum indicated human dose. No teratogenic potential was observed in any of these species.

There are no adequate and well-controlled studies in pregnant women. Nadolol should be used during pregnancy only if the potential benefit justifies the potential risk to the fetus. Neonates whose mothers are receiving nadolol at parturition have exhibited bradycardia, hypoglycemia, and associated symptoms.

NURSING MOTHERS

Nadolol is excreted in human milk. Because of the potential for adverse effects in nursing infants, a decision should be made whether to discontinue nursing or to discontinue therapy taking into account the importance of nadolol to the mother.

PEDIATRIC USE

Safety and effectiveness in pediatric patients have not been established.

ADVERSE REACTIONS

Most adverse effects have been mild and transient and have rarely required withdrawal of therapy.

Cardiovascular

Bradycardia with heart rates of less than 60 beats per minute occurs commonly, and heart rates below 40 beats per minute and/or symptomatic bradycardia were seen in about 2 of 100 patients. Symptoms of peripheral vascular insufficiency, usually of the Raynaud type, have occurred in approximately 2 of 100 patients. Cardiac failure, hypotension, and rhythm/conduction disturbances have each occurred in about 1 of 100 patients. Single instances of first degree and third degree heart block have been reported; intensification of AV block is a known effect of beta-blockers (see also CONTRAINDICATIONS, WARNINGS, and PRECAUTIONS).

Central Nervous System

Dizziness or fatigue has been reported in approximately 2 of 100 patients; paresthesias, sedation, and change in behavior have each been reported in approximately 6 of 1000 patients.

Respiratory

Bronchospasm has been reported in approximately 1 of 1000 patients (see CONTRAINDICATIONS and WARNINGS).

Gastrointestinal

Nausea, diarrhea, abdominal discomfort, constipation, vomiting, indigestion, anorexia, bloating, and flatulence have been reported in 1 to 5 of 1000 patients.

Miscellaneous

Each of the following has been reported in 1 to 5 of 1000 patients: rash; pruritus; headache; dry mouth, eyes, or skin; impotence or decreased libido; facial swelling; weight gain; slurred speech; cough; nasal stuffiness; sweating; tinnitus; blurred vision. Reversible alopecia has been reported infrequently.

The following adverse reactions have been reported in patients taking nadolol and/or other beta-adrenergic blocking agents, but no causal relationship to nadolol has been established.

Central Nervous System

Reversible mental depression progressing to catatonia; visual disturbances; hallucinations; an acute reversible syndrome characterized by disorientation for time and place, short-term memory loss, emotional lability with slightly clouded sensorium, and decreased performance on neuropsychometrics.

Gastrointestinal

Mesenteric arterial thrombosis; ischemic colitis; elevated liver enzymes.

Hematologic

Agranulocytosis; thrombocytopenic or nonthrombocytopenic purpura.

Allergic

Fever combined with aching and sore throat; laryngospasm; respiratory distress.

Miscellaneous

Pemphigoid rash; hypertensive reaction in patients with pheochromocytoma; sleep disturbances; Peyronie's disease.

The oculomucocutaneous syndrome associated with the beta-blocker practolol has not been reported with nadolol.
To report SUSPECTED ADVERSE REACTIONS, contact Aurobindo Pharma USA, Inc. at 1-866-850-2876 or FDA at 1-800-FDA-1088 or www.fda.gov/medwatch.

OVERDOSAGE

Nadolol can be removed from the general circulation by hemodialysis.

In addition to gastric lavage, the following measures should be employed, as appropriate. In determining the duration of corrective therapy, note must be taken of the long duration of the effect of nadolol.

Excessive Bradycardia

Administer atropine (0.25 to 1 mg). If there is no response to vagal blockade, administer isoproterenol cautiously.

Cardiac Failure

Administer a digitalis glycoside and diuretic. It has been reported that glucagon may also be useful in this situation.

Hypotension

Administer vasopressors, e.g., epinephrine or norepinephrine. (There is evidence that epinephrine may be the drug of choice.)

Bronchospasm

Administer a beta2-stimulating agent and/or a theophylline derivative.

DOSAGE AND ADMINISTRATION

DOSAGE MUST BE INDIVIDUALIZED. NADOLOL MAY BE ADMINISTERED WITHOUT REGARD TO MEALS.

Angina Pectoris

The usual initial dose is 40 mg nadolol once daily. Dosage may be gradually increased in 40 to 80 mg increments at 3 to 7 day intervals until optimum clinical response is obtained or there is pronounced slowing of the heart rate. The usual maintenance dose is 40 or 80 mg administered once daily. Doses up to 160 or 240 mg administered once daily may be needed.

The usefulness and safety in angina pectoris of dosage exceeding 240 mg per day have not been established. If treatment is to be discontinued, reduce the dosage gradually over a period of one to two weeks (see WARNINGS).

Hypertension

The usual initial dose is 40 mg nadolol once daily, whether it is used alone or in addition to diuretic therapy. Dosage may be gradually increased in 40 to 80 mg increments until optimum blood pressure reduction is achieved. The usual maintenance dose is 40 or 80 mg administered once daily. Doses up to 240 or 320 mg administered once daily may be needed.

Dosage Adjustment in Renal Failure

Absorbed nadolol is excreted principally by the kidneys and, although nonrenal elimination does occur, dosage adjustments are necessary in patients with renal impairment. The following dose intervals are recommended:

Creatinine Clearance (mL/min/1.73 m^2) | Dosage Interval (hours)
>50 | 24
31 to 50 | 24 to 36
10 to 30 | 24 to 48
<10 | 40 to 60

HOW SUPPLIED

Nadolol Tablets USP, 20 mgare light blue colored, round, uncoated mottled tablets with scoreline on one side and ‘NA’ and ‘20’ debossed on one side. They are supplied as follows:
NDC 68001-690-00 bottles of 100

Nadolol Tablets USP, 40 mgare light blue colored, round, biconvex, uncoated mottled tablets with scoreline separating ‘NA’ and ‘40’ debossed on one side and plain on other side. They are supplied as follows:
NDC 68001-691-00 bottles of 100

Nadolol Tablets USP, 80 mgare light blue colored, round, biconvex, uncoated mottled tablets with scoreline separating ‘NA’ and ‘80’ debossed on one side and plain on other side. They are supplied as follows:
NDC 68001-692-00 bottles of 100

STORAGE

Store at 20° to 25°C (68° to 77°F) [see USP Controlled Room Temperature]. Protect from light. Keep container tightly closed.

Manufactured by:
Aurobindo Pharma Limited
Hyderabad-500 090, India

For BluePoint Laboratories

M. L .No.: 19/HD/AP/95/F/R

Issued: 11/2025

PACKAGE LABEL.PRINCIPAL DISPLAY PANEL - 20 mg (100 Tablets Bottle)

NDC 68001-690-00

Rx only
Nadolo Tablets, USP 20 mg
100 Tablets

PACKAGE LABEL.PRINCIPAL DISPLAY PANEL - 40 mg (100 Tablets Bottle)

NDC 68001-691-00
Rx only
Nadolo Tablets, USP 40 mg

100 Tablets

PACKAGE LABEL.PRINCIPAL DISPLAY PANEL - 80 mg (100 Tablets Bottle)

NDC 68001-692-00
Rx only
Nadolo Tablets, USP 80 mg
100 Tablets